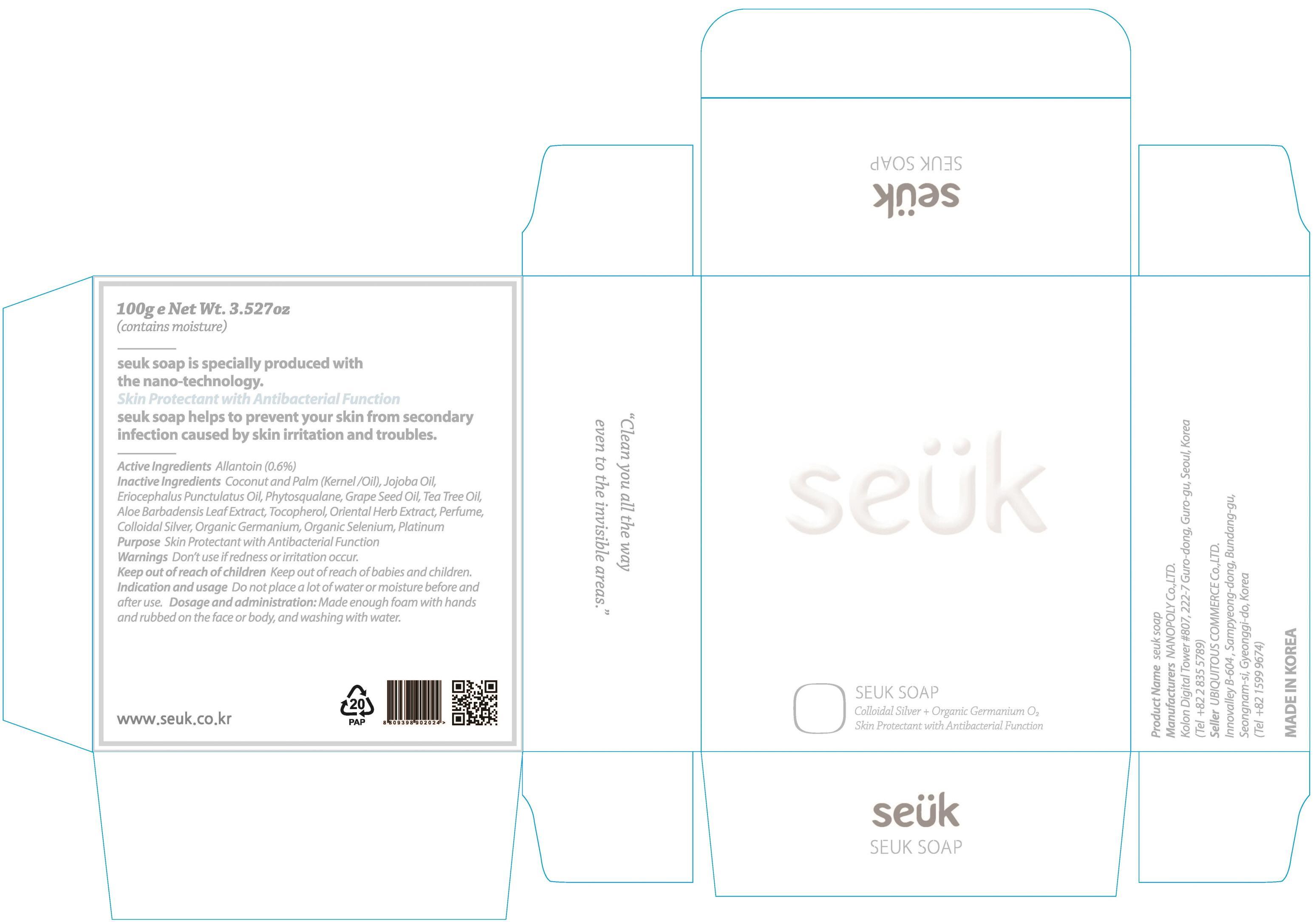 DRUG LABEL: SEUK
NDC: 54170-130 | Form: SOAP
Manufacturer: NANOPOLY CO., LTD.
Category: otc | Type: HUMAN OTC DRUG LABEL
Date: 20140326

ACTIVE INGREDIENTS: Allantoin 0.6 g/100 g
INACTIVE INGREDIENTS: COCONUT OIL; JOJOBA OIL

ACTIVE INGREDIENT

Active ingredient: Allantoin 0.6%

INACTIVE INGREDIENT

Inactive ingredients:
Coconut and Palm (Kernel/Oil), Jojoba Oil, Eriocephalus Punctulatus Oil, Phytosqualane, Grape Seed Oil, Tea Tree Oil, Aloe Barbadensis Leaf Extract, Tocopherol, Oriental Herb Extract, Perfume, Colloidal Silver, Organic Germanium, Organic Selenium, Platinum

PURPOSE

Purpose: Skin Protectant

WARNINGS

Warnings: Don't use if redness or irritation occur.

Keep out of reach of children: Keep out of reach of babies and children.

INDICATIONS AND USAGE

Indication and usage: Do not place a lot of water or moisture before and after use.

Dosage and administration: Made enough foam with hands and rubbed on the face or body, and washing with water.